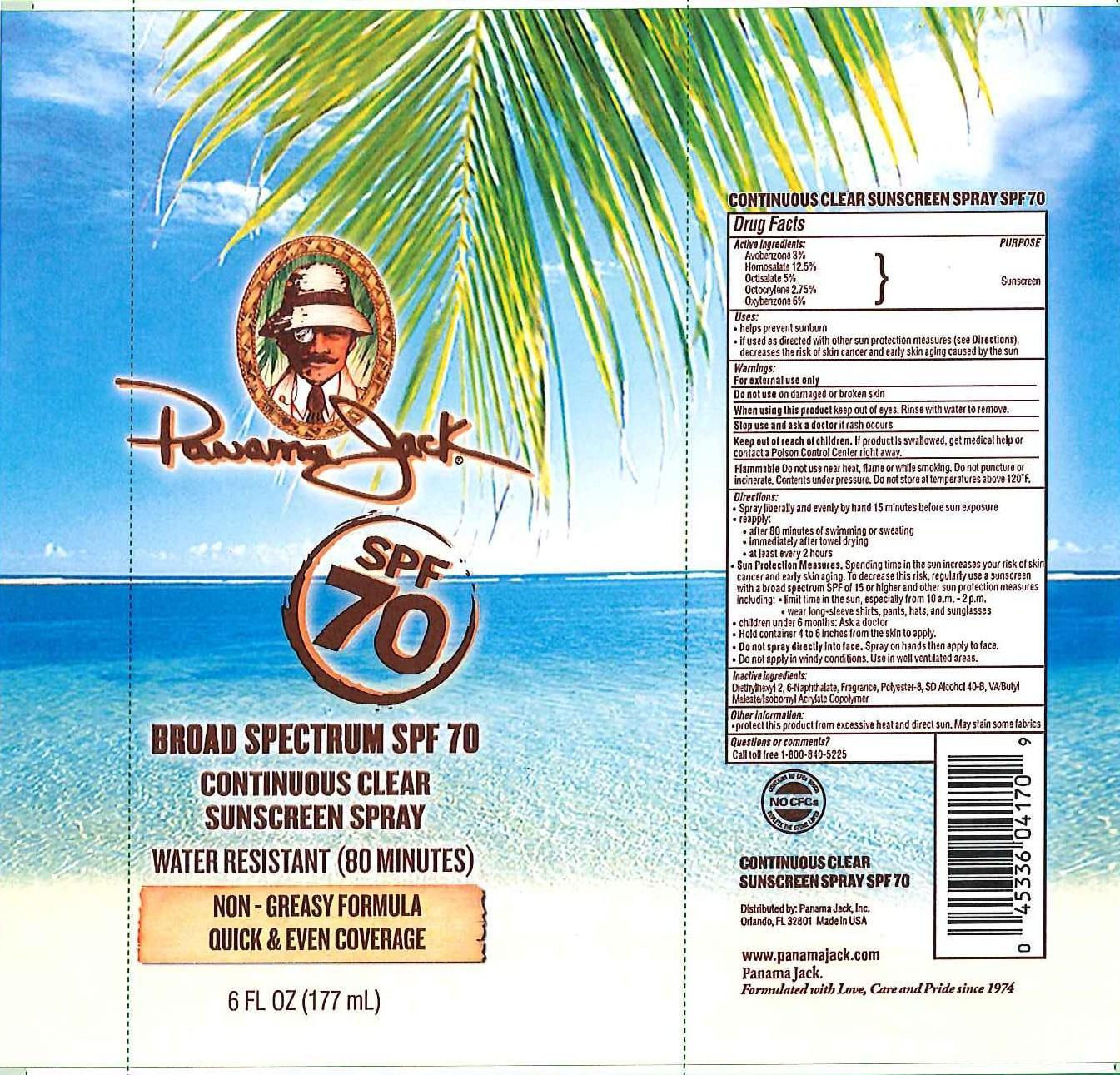 DRUG LABEL: Panama Jack
NDC: 13630-0036 | Form: SPRAY
Manufacturer: Prime Packaging, Inc.
Category: otc | Type: HUMAN OTC DRUG LABEL
Date: 20200117

ACTIVE INGREDIENTS: AVOBENZONE 25.6 mg/1 mL; HOMOSALATE 106.8 mg/1 mL; OCTISALATE 42.7 mg/1 mL; OCTOCRYLENE 23.5 mg/1 mL; OXYBENZONE 51.2 mg/1 mL
INACTIVE INGREDIENTS: DIETHYLHEXYL 2,6-NAPHTHALATE; ALCOHOL; POLYESTER-8 (1400 MW, CYANODIPHENYLPROPENOYL CAPPED)

Active ingredients

Avobenzone 3 %, Homosalate 12.5 %, Octisalate 5 %, Octocrylene 2.75 %, Oxybenzone 6 %

Purpose

Sunscreen

Uses

- helps prevent sunburn
- if used as directed with other sun protection measures (see Directions), decreases the risk of skin cancer and early skin aging caused by the sun

Warnings

OTHER SAFETY INFORMATION

For external use only

Do not use on damaged or broken skin.

When using this product keep out of eyes. Rinse with water to remove.

Stop use and ask a doctor if rash occurs.

Keep out of reach of children. If product is swallowed, get medical help or contact a Poison Control Center right away.

OTHER SAFETY INFORMATION

Flammable: Do not use near heat, flame or while smoking. Do not puncture or incinerate. Contents under pressure. Do not store at temperatures above 120^0F

Directions

- spray liberally and spread by hand 15 minutes before sun exposure
- reapply:
  - after 80 minutes of swimming or sweating
  - immediately after towel drying
  - at least every 2 hours
- Sun Protection Measures. Spending time in the sun increases your risk of skin cancer and early skin aging. To decrease this risk, regularly use a sunscreen with broad spectrum SPF of 15 or higher and other sun protection measures including:
  - limit time in the sun, especially from 10 a.m. – 2 p.m.
  - wear long-sleeve shirts, pants, hats, and sunglasses
- children under 6 months: Ask a doctor
- Hold container 4 to 6 inches from the skin to apply
- Do not spray directly into face. Spray on hands then apply to face.
- Do not apply in windy conditions. Use in well ventilated areas.

Inactive Ingredients

Diethylhexyl 2,6-Naphthalate, Fragrance, Polyester-8, SD Alcohol 40-B, VA/Butyl Maleate/Isobornyl Acrylate Copolymer

Other information

- protect this product from excesive heat and direct sun. May stain some fabrics

Questions or Comments?

Call toll free 1-800-840-5225

PRINCIPAL DISPLAY PANEL - 177 mL Can Label

Panama Jack

SPF

70

BROAD SPECTRUM SPF 70

CONTINUOUS CLEAR

SUNSCREEN SPRAY

WATER RESISTANT (80 MINUTES)

NON-GREASY FORMULA

QUICK & EVEN COVERAGE

6 FL OZ (177 mL)